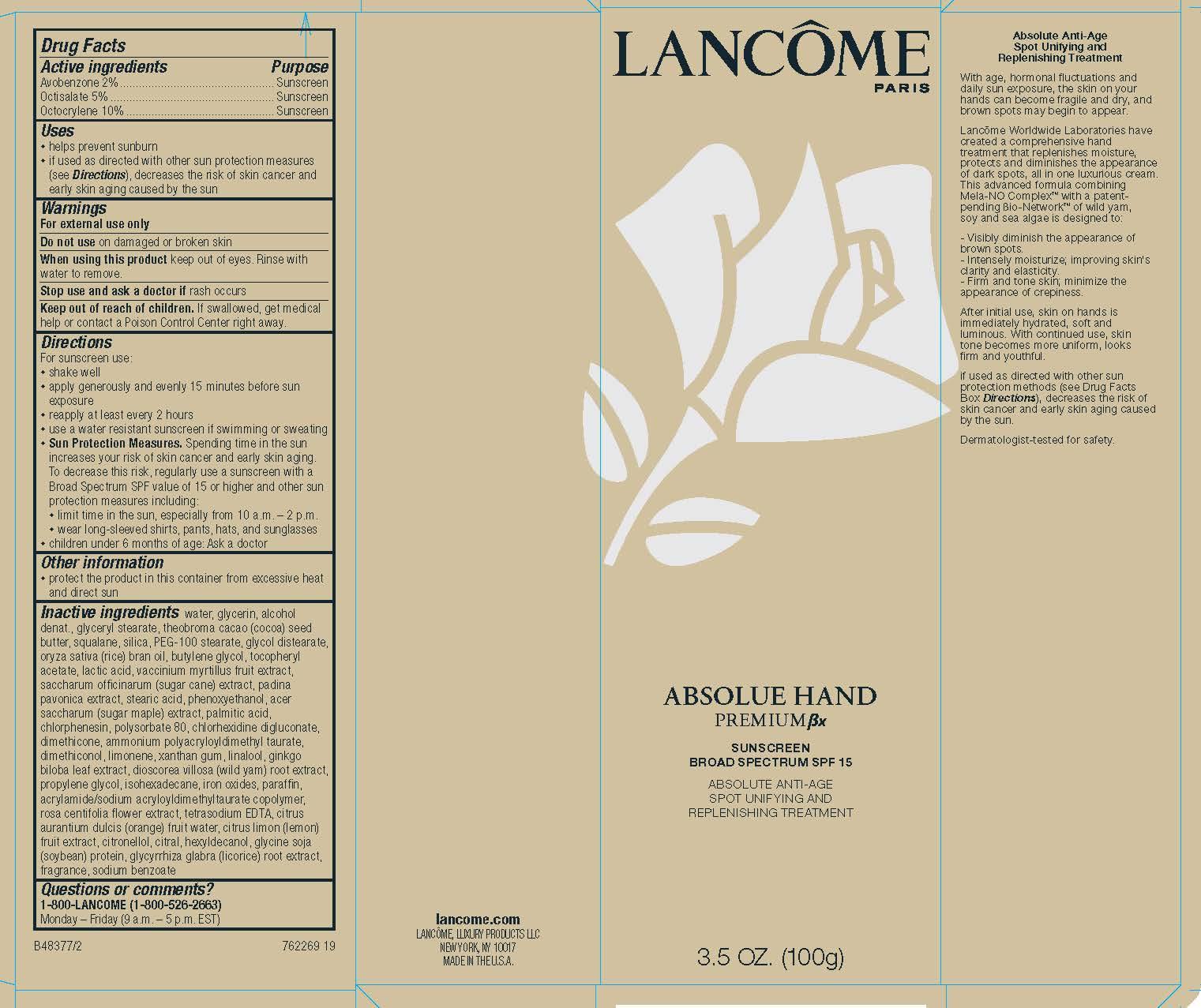 DRUG LABEL: Lancome Paris Absolue Hand Premium Bx Broad Spectrum SPF 15 Sunscreen Absolute Anti Age Spot Unifying And Replenishing Treatment
NDC: 49967-137 | Form: LOTION
Manufacturer: L'Oreal USA Products Inc
Category: otc | Type: HUMAN OTC DRUG LABEL
Date: 20231230

ACTIVE INGREDIENTS: AVOBENZONE 20 mg/1 g; OCTISALATE 50 mg/1 g; OCTOCRYLENE 100 mg/1 g
INACTIVE INGREDIENTS: WATER; GLYCERIN; ALCOHOL; SODIUM BENZOATE

Drug Facts

Active ingredients

Avobenzone 2%

Octisalate 5%

Octocrylene 10%

Purpose

Sunscreen

Uses

- helps prevent sunburn
- if used as directed with other sun protection measures (see Directions), decreases the risk of skin cancer and early skin aging caused by the sun

Warnings

For external use only

Do not use

on damaged or broken skin

When using this product

keep out of eyes. Rinse with water to remove.

Stop use and ask a doctor if

rash occurs

Keep out of reach of children.

If swallowed, get medical help or contact a Poison Control Center right away.

Directions

For sunscreen use:

● shake well

● apply generously and evenly 15minutes before sun exposure

● reapply at least every 2 hours

● use a water resistant sunscreen if swimming or sweating

● Sun Protection Measures. Spending time in the sun increases your risk of skin cancer and early skin aging. To decrease this risk, regularly use a sunscreen with a Broad Spectrum SPF value of 15 or higher and other sun protection measures including:

● limit time in the sun, especially from 10 a.m. – 2 p.m.

● wear long-sleeved shirts, pants, hats, and sunglasses

● children under 6 months of age: Ask a doctor

Other information

protect the product in this container from excessive heat and direct sun

Inactive ingredients

water, glycerin, alcohol denat., glyceryl stearate, theobroma cacao (cocoa) seed butter, squalane, silica, PEG-100 stearate, glycol distearate, oryza sativa (rice) bran oil, butylene glycol, tocopheryl acetate, lactic acid, vaccinium myrtillus fruit extract, saccharum officinarum (sugar cane) extact, padina pavonica extract, stearic acid, pehnoxyethanol, acer saccharum (sugar maple) extract, palmitic acid, chlorphenesin, polysorbate 80, chlorhexidine digluconate, dimethicone, ammonium polyacryloyldimethyl taurate, dimethiconol, limonene, xanthan gum, linalool, ginkgo biloba leaf extract, dioscorea villosa (wild yam) root extract, propylene glycol, isohexadecane, iron oxides, paraffin, acrylamide/sodium acryloyldimethyltaurate copolymer, rosa centifolia flower extract, tetrasodium EDTA, citrus aurantium dulcis (orange) fruit water, citrus limon (lemon) fruit extract, citronellol, citral, hexyldecanol, glycine soja (soybean) protein, glycyrrhiza glabra (licorice) root extrract, fragrance, sodium benzoate

Questions or comments?

1-800-LANCOME (1-800-526-2663)

Monday - Friday (9 a.m. - 5 p.m. EST)